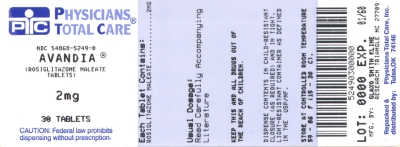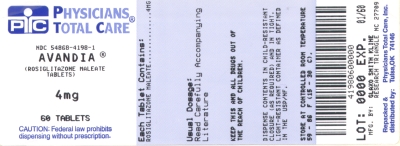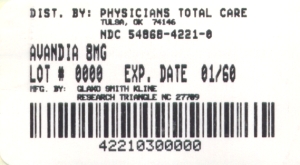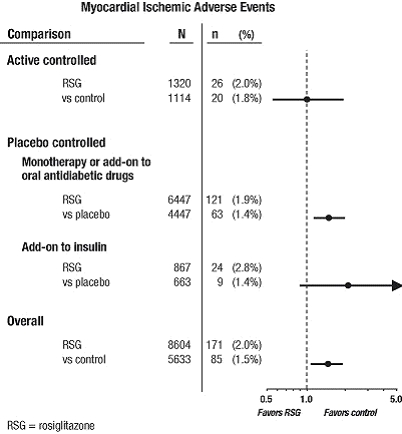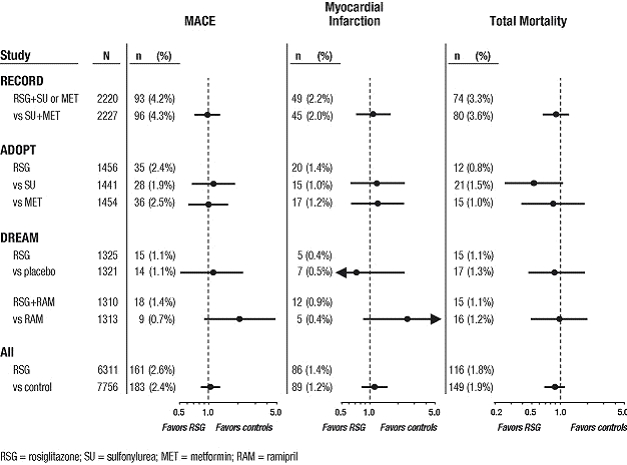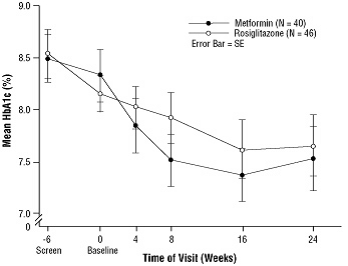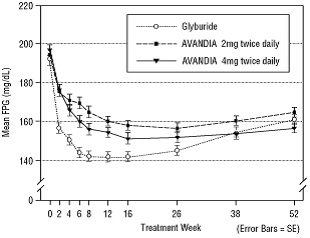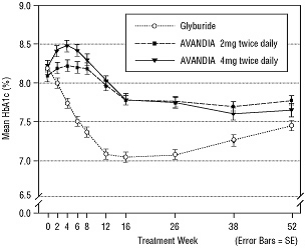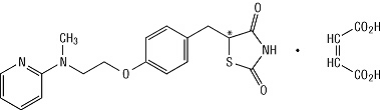 DRUG LABEL: Avandia
NDC: 54868-5249 | Form: TABLET, FILM COATED
Manufacturer: Physicians Total Care, Inc.
Category: prescription | Type: HUMAN PRESCRIPTION DRUG LABEL
Date: 20100119

ACTIVE INGREDIENTS: ROSIGLITAZONE MALEATE 2 mg/1 1
INACTIVE INGREDIENTS: HYPROMELLOSE 2910 (3 CPS); LACTOSE MONOHYDRATE; MAGNESIUM STEARATE; CELLULOSE, MICROCRYSTALLINE; POLYETHYLENE GLYCOL 3000; SODIUM STARCH GLYCOLATE TYPE A POTATO; TITANIUM DIOXIDE; TRIACETIN; TALC; FERRIC OXIDE RED; FERRIC OXIDE YELLOW

FULL PRESCRIBING INFORMATION

WARNING: CONGESTIVE HEART FAILURE AND MYOCARDIAL ISCHEMIA

- Thiazolidinediones, including rosiglitazone, cause or exacerbate congestive heart failure in some patients [see Warnings and Precautions (5.1)]. After initiation of AVANDIA, and after dose increases, observe patients carefully for signs and symptoms of heart failure (including excessive, rapid weight gain, dyspnea, and/or edema). If these signs and symptoms develop, the heart failure should be managed according to current standards of care. Furthermore, discontinuation or dose reduction of AVANDIA must be considered.
- AVANDIA is not recommended in patients with symptomatic heart failure. Initiation of AVANDIA in patients with established NYHA Class III or IV heart failure is contraindicated. [See Contraindications (4) and Warnings and Precautions (5.1).]
- A meta-analysis of 42 clinical studies (mean duration 6 months; 14,237 total patients), most of which compared AVANDIA to placebo, showed AVANDIA to be associated with an increased risk of myocardial ischemic events such as angina or myocardial infarction. Three other studies (mean duration 41 months; 14,067 total patients), comparing AVANDIA to some other approved oral antidiabetic agents or placebo, have not confirmed or excluded this risk. In their entirety, the available data on the risk of myocardial ischemia are inconclusive. [See Warnings and Precautions (5.2).]

1 INDICATIONS AND USAGE

1.1 Monotherapy and Combination Therapy

AVANDIA is indicated as an adjunct to diet and exercise to improve glycemic control in adults with type 2 diabetes mellitus.

1.2 Important Limitations of Use

- Due to its mechanism of action, AVANDIA is active only in the presence of endogenous insulin. Therefore, AVANDIA should not be used in patients with type 1 diabetes mellitus or for the treatment of diabetic ketoacidosis.
- The coadministration of AVANDIA and insulin is not recommended.
- The use of AVANDIA with nitrates is not recommended.

2 DOSAGE AND ADMINISTRATION

The management of antidiabetic therapy should be individualized. All patients should start AVANDIA at the lowest recommended dose. Further increases in the dose of AVANDIA should be accompanied by careful monitoring for adverse events related to fluid retention [see Boxed Warning and Warnings and Precautions (5.1)].

AVANDIA may be administered at a starting dose of 4 mg either as a single daily dose or in 2 divided doses. For patients who respond inadequately following 8 to 12 weeks of treatment, as determined by reduction in fasting plasma glucose (FPG), the dose may be increased to 8 mg daily as monotherapy or in combination with metformin, sulfonylurea, or sulfonylurea plus metformin. Reductions in glycemic parameters by dose and regimen are described under Clinical Studies (14.1). AVANDIA may be taken with or without food.

The total daily dose of AVANDIA should not exceed 8 mg.

2.1 Monotherapy

The usual starting dose of AVANDIA is 4 mg administered either as a single dose once daily or in divided doses twice daily. In clinical trials, the 4-mg twice-daily regimen resulted in the greatest reduction in FPG and hemoglobin A1c (HbA1c).

2.2 Combination With Sulfonylurea or Metformin

When AVANDIA is added to existing therapy, the current dose(s) of the agent(s) can be continued upon initiation of therapy with AVANDIA.

Sulfonylurea

When used in combination with sulfonylurea, the usual starting dose of AVANDIA is 4 mg administered as either a single dose once daily or in divided doses twice daily. If patients report hypoglycemia, the dose of the sulfonylurea should be decreased.

Metformin

The usual starting dose of AVANDIA in combination with metformin is 4 mg administered as either a single dose once daily or in divided doses twice daily. It is unlikely that the dose of metformin will require adjustment due to hypoglycemia during combination therapy with AVANDIA.

2.3 Combination With Sulfonylurea Plus Metformin

The usual starting dose of AVANDIA in combination with a sulfonylurea plus metformin is 4 mg administered as either a single dose once daily or divided doses twice daily. If patients report hypoglycemia, the dose of the sulfonylurea should be decreased.

2.4 Specific Patient Populations

Renal Impairment

No dosage adjustment is necessary when AVANDIA is used as monotherapy in patients with renal impairment. Since metformin is contraindicated in such patients, concomitant administration of metformin and AVANDIA is also contraindicated in patients with renal impairment.

Hepatic Impairment

Liver enzymes should be measured prior to initiating treatment with AVANDIA. Therapy with AVANDIA should not be initiated if the patient exhibits clinical evidence of active liver disease or increased serum transaminase levels (ALT >2.5X upper limit of normal at start of therapy). After initiation of AVANDIA, liver enzymes should be monitored periodically per the clinical judgment of the healthcare professional. [See Warnings and Precautions (5.6) and Clinical Pharmacology (12.3).]

Pediatric

Data are insufficient to recommend pediatric use of AVANDIA [see Use in Specific Populations (8.4)].

3 DOSAGE FORMS AND STRENGTHS

Pentagonal film-coated TILTAB® tablet contains rosiglitazone as the maleate as follows:

- 2 mg - pink, debossed with SB on one side and 2 on the other
- 4 mg - orange, debossed with SB on one side and 4 on the other
- 8 mg - red-brown, debossed with SB on one side and 8 on the other

4 CONTRAINDICATIONS

Initiation of AVANDIA in patients with established New York Heart Association (NYHA) Class III or IV heart failure is contraindicated [see Boxed Warning].

5 WARNINGS AND PRECAUTIONS

5.1 Cardiac Failure

AVANDIA, like other thiazolidinediones, alone or in combination with other antidiabetic agents, can cause fluid retention, which may exacerbate or lead to heart failure. Patients should be observed for signs and symptoms of heart failure. If these signs and symptoms develop, the heart failure should be managed according to current standards of care. Furthermore, discontinuation or dose reduction of rosiglitazone must be considered [see Boxed Warning].

Patients with congestive heart failure (CHF) NYHA Class I and II treated with AVANDIA have an increased risk of cardiovascular events. A 52-week, double-blind, placebo-controlled echocardiographic study was conducted in 224 patients with type 2 diabetes mellitus and NYHA Class I or II CHF (ejection fraction ≤45%) on background antidiabetic and CHF therapy. An independent committee conducted a blinded evaluation of fluid-related events (including congestive heart failure) and cardiovascular hospitalizations according to predefined criteria (adjudication). Separate from the adjudication, other cardiovascular adverse events were reported by investigators. Although no treatment difference in change from baseline of ejection fractions was observed, more cardiovascular adverse events were observed following treatment with AVANDIA compared to placebo during the 52-week study. (See Table 1.)

Table 1. Emergent Cardiovascular Adverse Events in Patients With Congestive Heart Failure (NYHA Class I and II) Treated With AVANDIA or Placebo (in Addition to Background Antidiabetic and CHF Therapy)
Events | AVANDIA | Placebo
 | N = 110; n (%) | N = 114; n (%)
Adjudicated
Cardiovascular deaths | 5 (5%) | 4 (4%)
CHF worsening | 7 (6%) | 4 (4%)
- with overnight hospitalization | 5 (5%) | 4 (4%)
- without overnight hospitalization | 2 (2%) | 0 (0%)
New or worsening edema | 28 (25%) | 10 (9%)
New or worsening dyspnea | 29 (26%) | 19 (17%)
Increase in CHF medication | 36 (33%) | 20 (18%)
Cardiovascular hospitalization* | 21 (19%) | 15 (13%)
Investigator-reported, non-adjudicated
Ischemic adverse events | 10 (9%) | 5 (4%)
- Myocardial infarction | 5 (5%) | 2 (2%)
- Angina | 6 (5%) | 3 (3%)
* Includes hospitalization for any cardiovascular reason.

Initiation of AVANDIA in patients with established NYHA Class III or IV heart failure is contraindicated. AVANDIA is not recommended in patients with symptomatic heart failure. [See Boxed Warning.]

Patients experiencing acute coronary syndromes have not been studied in controlled clinical trials. In view of the potential for development of heart failure in patients having an acute coronary event, initiation of AVANDIA is not recommended for patients experiencing an acute coronary event, and discontinuation of AVANDIA during this acute phase should be considered.

Patients with NYHA Class III and IV cardiac status (with or without CHF) have not been studied in controlled clinical trials. AVANDIA is not recommended in patients with NYHA Class III and IV cardiac status.

5.2 Myocardial Ischemia

Meta-Analysis of Myocardial Ischemia in a Group of 42 Clinical Trials

A meta-analysis was conducted retrospectively to assess cardiovascular adverse events reported across 42 double-blind, randomized, controlled clinical trials (mean duration 6 months).^1 These studies had been conducted to assess glucose-lowering efficacy in type 2 diabetes, and prospectively planned adjudication of cardiovascular events had not occurred in the trials. Some trials were placebo-controlled and some used active oral antidiabetic drugs as controls. Placebo-controlled studies included monotherapy trials (monotherapy with AVANDIA versus placebo monotherapy) and add-on trials (AVANDIA or placebo, added to sulfonylurea, metformin, or insulin). Active control studies included monotherapy trials (monotherapy with AVANDIA versus sulfonylurea or metformin monotherapy) and add-on trials (AVANDIA plus sulfonylurea or AVANDIA plus metformin, versus sulfonylurea plus metformin). A total of 14,237 patients were included (8,604 in treatment groups containing AVANDIA, 5,633 in comparator groups), with 4,143 patient-years of exposure to AVANDIA and 2,675 patient-years of exposure to comparator. Myocardial ischemic events included angina pectoris, angina pectoris aggravated, unstable angina, cardiac arrest, chest pain, coronary artery occlusion, dyspnea, myocardial infarction, coronary thrombosis, myocardial ischemia, coronary artery disease, and coronary artery disorder. In this analysis, an increased risk of myocardial ischemia with AVANDIA versus pooled comparators was observed (2% AVANDIA versus 1.5% comparators, odds ratio 1.4, 95% confidence interval [CI] 1.1, 1.8). An increased risk of myocardial ischemic events with AVANDIA was observed in the placebo-controlled studies, but not in the active-controlled studies. (See Figure 1.)

A greater increased risk of myocardial ischemic events was observed in studies where AVANDIA was added to insulin (2.8% for AVANDIA plus insulin versus 1.4% for placebo plus insulin, [OR 2.1, 95% CI 0.9, 5.1]). This increased risk reflects a difference of 3 events per 100 patient-years (95% CI -0.1, 6.3) between treatment groups. [See Warnings and Precautions (5.3).]

Figure 1. Forest Plot of Odds Ratios (95% Confidence Intervals) for Myocardial Ischemic Events in the Meta-Analysis of 42 Clinical Trials

A greater increased risk of myocardial ischemia was also observed in patients who received AVANDIA and background nitrate therapy. For AVANDIA (N = 361) versus control (N = 244) in nitrate users, the odds ratio was 2.9 (95% CI 1.4, 5.9), while for non-nitrate users (about 14,000 patients total), the odds ratio was 1.3 (95% CI 0.9, 1.7). This increased risk represents a difference of 12 myocardial ischemic events per 100 patient-years (95% CI 3.3, 21.4). Most of the nitrate users had established coronary heart disease. Among patients with known coronary heart disease who were not on nitrate therapy, an increased risk of myocardial ischemic events for AVANDIA versus comparator was not demonstrated.

Myocardial Ischemic Events in Large, Long-Term, Prospective, Randomized, Controlled Trials of AVANDIA

Data from 3 other large, long-term, prospective, randomized, controlled clinical trials of AVANDIA were assessed separately from the meta-analysis. These 3 trials include a total of 14,067 patients (treatment groups containing AVANDIA N = 6,311, comparator groups N = 7,756), with patient-year exposure of 21,803 patient-years for AVANDIA and 25,998 patient-years for comparator. Duration of follow-up exceeded 3 years in each study. ADOPT (A Diabetes Outcomes Progression Trial) was a 4- to 6-year randomized, active-controlled study in recently diagnosed patients with type 2 diabetes naïve to drug therapy. It was an efficacy and general safety trial that was designed to examine the durability of AVANDIA as monotherapy (N = 1,456) for glycemic control in type 2 diabetes, with comparator arms of sulfonylurea monotherapy (N = 1,441) and metformin monotherapy (N = 1,454). DREAM (Diabetes Reduction Assessment with Rosiglitazone and Ramipril Medication, published report^2) was a 3- to 5-year randomized, placebo-controlled study in patients with impaired glucose tolerance and/or impaired fasting glucose. It had a 2x2 factorial design, intended to evaluate the effect of AVANDIA, and separately of ramipril (an angiotensin converting enzyme inhibitor [ACEI]), on progression to overt diabetes. In DREAM, 2,635 patients were in treatment groups containing AVANDIA, and 2,634 were in treatment groups not containing AVANDIA. Interim results have been published^3 for RECORD (Rosiglitazone Evaluated for Cardiac Outcomes and Regulation of Glycemia in Diabetes), an ongoing open-label, 6-year cardiovascular outcomes study in patients with type 2 diabetes with an average treatment duration of 3.75 years. RECORD includes patients who have failed metformin or sulfonylurea monotherapy; those who have failed metformin are randomized to receive either add-on AVANDIA or add-on sulfonylurea, and those who have failed sulfonylurea are randomized to receive either add-on AVANDIA or add-on metformin. In RECORD, a total of 2,220 patients are receiving add-on AVANDIA, and 2,227 patients are on one of the add-on regimens not containing AVANDIA.

For these 3 trials, analyses were performed using a composite of major adverse cardiovascular events (myocardial infarction, cardiovascular death, or stroke), referred to hereafter as MACE. This endpoint differed from the meta-analysis’ broad endpoint of myocardial ischemic events, more than half of which were angina. Myocardial infarction included adjudicated fatal and nonfatal myocardial infarction plus sudden death. As shown in Figure 2, the results for the 3 endpoints (MACE, MI, and Total Mortality) were not statistically significantly different between AVANDIA and comparators.

Figure 2. Hazard Ratios for the Risk of MACE (Myocardial Infarction, Cardiovascular Death, or Stroke), Myocardial Infarction, and Total Mortality With AVANDIA Compared With a Control Group

In preliminary analyses of the DREAM trial, the incidence of cardiovascular events was higher among subjects who received AVANDIA in combination with ramipril than among subjects who received ramipril alone, as illustrated in Figure 2. This finding was not confirmed in ADOPT and RECORD (active-controlled trials in patients with diabetes) in which 30% and 40% of patients respectively, reported ACE-inhibitor use at baseline.

In their entirety, the available data on the risk of myocardial ischemia are inconclusive. Definitive conclusions regarding this risk await completion of an adequately-designed cardiovascular outcome study.

There have been no clinical studies establishing conclusive evidence of macrovascular risk reduction with AVANDIA or any other oral antidiabetic drug.

5.3 Congestive Heart Failure and Myocardial Ischemia During Coadministration of AVANDIA With Insulin

In studies in which AVANDIA was added to insulin, AVANDIA increased the risk of congestive heart failure and myocardial ischemia. (See Table 2.) Coadministration of AVANDIA and insulin is not recommended. [See Indications and Usage (1.2) and Warnings and Precautions (5.1, 5.2).]

In five, 26-week, controlled, randomized, double-blind trials which were included in the meta-analysis [see Warnings and Precautions (5.2)], patients with type 2 diabetes mellitus were randomized to coadministration of AVANDIA and insulin (N = 867) or insulin (N = 663). In these 5 trials, AVANDIA was added to insulin. These trials included patients with long-standing diabetes (median duration of 12 years) and a high prevalence of pre-existing medical conditions, including peripheral neuropathy, retinopathy, ischemic heart disease, vascular disease, and congestive heart failure. The total number of patients with emergent congestive heart failure was 21 (2.4%) and 7 (1.1%) in the AVANDIA plus insulin and insulin groups, respectively. The total number of patients with emergent myocardial ischemia was 24 (2.8%) and 9 (1.4%) in the AVANDIA plus insulin and insulin groups, respectively (OR 2.1 [95% CI 0.9, 5.1]). Although the event rate for congestive heart failure and myocardial ischemia was low in the studied population, consistently the event rate was 2-fold or higher with coadministration of AVANDIA and insulin. These cardiovascular events were noted at both the 4 mg and 8 mg daily doses of AVANDIA. (See Table 2.)

Table 2. Occurrence of Cardiovascular Events in 5 Controlled Trials of Addition of AVANDIA to Established Insulin Treatment
Event* | AVANDIA + Insulin (n = 867) n (%) | Insulin (n = 663) n (%)
Congestive heart failure | 21 (2.4%) | 7 (1.1%)
Myocardial ischemia | 24 (2.8%) | 9 (1.4%)
Composite of cardiovascular death, myocardial infarction, or stroke | 10 (1.2%) | 5 (0.8%)
Stroke | 5 (0.6%) | 4 (0.6%)
Myocardial infarction | 4 (0.5%) | 1 (0.2%)
Cardiovascular death | 4 (0.5%) | 1 (0.2%)
All deaths | 6 (0.7%) | 1 (0.2%)

* Events are not exclusive; i.e., a patient with a cardiovascular death due to a myocardial infarction would be counted in 4 event categories (myocardial ischemia; cardiovascular death, myocardial infarction, or stroke; myocardial infarction; cardiovascular death).

In a sixth, 24-week, controlled, randomized, double-blind trial of AVANDIA and insulin coadministration, insulin was added to AVANDAMET® (rosiglitazone maleate and metformin HCl) (n = 161) and compared to insulin plus placebo (n = 158), after a single-blind 8-week run-in with AVANDAMET. Patients with edema requiring pharmacologic therapy and those with congestive heart failure were excluded at baseline and during the run-in period. In the group receiving AVANDAMET plus insulin, there was one myocardial ischemic event and one sudden death. No myocardial ischemia was observed in the insulin group, and no congestive heart failure was reported in either treatment group.

5.4 Edema

AVANDIA should be used with caution in patients with edema. In a clinical study in healthy volunteers who received 8 mg of AVANDIA once daily for 8 weeks, there was a statistically significant increase in median plasma volume compared to placebo.

Since thiazolidinediones, including rosiglitazone, can cause fluid retention, which can exacerbate or lead to congestive heart failure, AVANDIA should be used with caution in patients at risk for heart failure. Patients should be monitored for signs and symptoms of heart failure [see Boxed Warning, Warnings and Precautions (5.1), and Patient Counseling Information (17.1)].

In controlled clinical trials of patients with type 2 diabetes, mild to moderate edema was reported in patients treated with AVANDIA, and may be dose related. Patients with ongoing edema were more likely to have adverse events associated with edema if started on combination therapy with insulin and AVANDIA [see Adverse Reactions (6.1)].

5.5 Weight Gain

Dose-related weight gain was seen with AVANDIA alone and in combination with other hypoglycemic agents (Table 3). The mechanism of weight gain is unclear but probably involves a combination of fluid retention and fat accumulation.

In postmarketing experience, there have been reports of unusually rapid increases in weight and increases in excess of that generally observed in clinical trials. Patients who experience such increases should be assessed for fluid accumulation and volume-related events such as excessive edema and congestive heart failure [see Boxed Warning].

Table 3. Weight Changes (kg) From Baseline at Endpoint During Clinical Trials
 |  | Control Group | AVANDIA; 4 mg | AVANDIA; 8 mg
Monotherapy | Duration |  | Median; (25th, 75th percentile) | Median; (25th, 75th percentile) | Median; (25th, 75th percentile)
 | 26 weeks | placebo | -0.9 (-2.8, 0.9); N = 210 | 1.0 (-0.9, 3.6); N = 436 | 3.1 (1.1, 5.8); N = 439
 | 52 weeks | sulfonylurea | 2.0 (0, 4.0); N = 173 | 2.0 (-0.6, 4.0); N = 150 | 2.6 (0, 5.3); N = 157
Combination therapy
Sulfonylurea | 24-26 weeks | sulfonylurea | 0 (-1.0, 1.3); N = 1,155 | 2.2 (0.5, 4.0); N = 613 | 3.5 (1.4, 5.9); N = 841
Metformin | 26 weeks | metformin | -1.4 (-3.2, 0.2); N = 175 | 0.8 (-1.0, 2.6); N = 100 | 2.1 (0, 4.3); N = 184
Insulin | 26 weeks | insulin | 0.9 (-0.5, 2.7); N = 162 | 4.1 (1.4, 6.3); N = 164 | 5.4 (3.4, 7.3); N = 150
Sulfonylurea + metformin | 26 weeks | sulfonylurea + metformin | 0.2 (-1.2, 1.6); N = 272 | 2.5 (0.8, 4.6); N = 275 | 4.5 (2.4, 7.3); N = 276

In a 4- to 6-year, monotherapy, comparative trial (ADOPT) in patients recently diagnosed with type 2 diabetes not previously treated with antidiabetic medication [see Clinical Studies (14.1)], the median weight change (25th, 75th percentiles) from baseline at 4 years was 3.5 kg (0.0, 8.1) for AVANDIA, 2.0 kg (-1.0, 4.8) for glyburide, and -2.4 kg (-5.4, 0.5) for metformin.

In a 24-week study in pediatric patients aged 10 to 17 years treated with AVANDIA 4 to 8 mg daily, a median weight gain of 2.8 kg (25th, 75th percentiles: 0.0, 5.8) was reported.

5.6 Hepatic Effects

Liver enzymes should be measured prior to the initiation of therapy with AVANDIA in all patients and periodically thereafter per the clinical judgment of the healthcare professional. Therapy with AVANDIA should not be initiated in patients with increased baseline liver enzyme levels (ALT >2.5X upper limit of normal). Patients with mildly elevated liver enzymes (ALT levels ≤2.5X upper limit of normal) at baseline or during therapy with AVANDIA should be evaluated to determine the cause of the liver enzyme elevation. Initiation of, or continuation of, therapy with AVANDIA in patients with mild liver enzyme elevations should proceed with caution and include close clinical follow-up, including liver enzyme monitoring, to determine if the liver enzyme elevations resolve or worsen. If at any time ALT levels increase to >3X the upper limit of normal in patients on therapy with AVANDIA, liver enzyme levels should be rechecked as soon as possible. If ALT levels remain >3X the upper limit of normal, therapy with AVANDIA should be discontinued.

If any patient develops symptoms suggesting hepatic dysfunction, which may include unexplained nausea, vomiting, abdominal pain, fatigue, anorexia and/or dark urine, liver enzymes should be checked. The decision whether to continue the patient on therapy with AVANDIA should be guided by clinical judgment pending laboratory evaluations. If jaundice is observed, drug therapy should be discontinued. [See Adverse Reactions (6.2, 6.3).]

5.7 Macular Edema

Macular edema has been reported in postmarketing experience in some diabetic patients who were taking AVANDIA or another thiazolidinedione. Some patients presented with blurred vision or decreased visual acuity, but some patients appear to have been diagnosed on routine ophthalmologic examination. Most patients had peripheral edema at the time macular edema was diagnosed. Some patients had improvement in their macular edema after discontinuation of their thiazolidinedione. Patients with diabetes should have regular eye exams by an ophthalmologist, per the Standards of Care of the American Diabetes Association. Additionally, any diabetic who reports any kind of visual symptom should be promptly referred to an ophthalmologist, regardless of the patient’s underlying medications or other physical findings. [See Adverse Reactions (6.1).]

5.8 Fractures

In a 4- to 6-year comparative study (ADOPT) of glycemic control with monotherapy in drug-naïve patients recently diagnosed with type 2 diabetes mellitus, an increased incidence of bone fracture was noted in female patients taking AVANDIA. Over the 4- to 6-year period, the incidence of bone fracture in females was 9.3% (60/645) for AVANDIA versus 3.5% (21/605) for glyburide and 5.1% (30/590) for metformin. This increased incidence was noted after the first year of treatment and persisted during the course of the study. The majority of the fractures in the women who received AVANDIA occurred in the upper arm, hand, and foot. These sites of fracture are different from those usually associated with postmenopausal osteoporosis (e.g., hip or spine). No increase in fracture rates was observed in men treated with AVANDIA. The risk of fracture should be considered in the care of patients, especially female patients, treated with AVANDIA, and attention given to assessing and maintaining bone health according to current standards of care.

5.9 Hematologic Effects

Decreases in mean hemoglobin and hematocrit occurred in a dose-related fashion in adult patients treated with AVANDIA [see Adverse Reactions (6.2)]. The observed changes may be related to the increased plasma volume observed with treatment with AVANDIA.

5.10 Diabetes and Blood Glucose Control

Patients receiving AVANDIA in combination with other hypoglycemic agents may be at risk for hypoglycemia, and a reduction in the dose of the concomitant agent may be necessary.

Periodic fasting blood glucose and HbA1c measurements should be performed to monitor therapeutic response.

5.11 Ovulation

Therapy with AVANDIA, like other thiazolidinediones, may result in ovulation in some premenopausal anovulatory women. As a result, these patients may be at an increased risk for pregnancy while taking AVANDIA [see Use in Specific Populations (8.1)]. Thus, adequate contraception in premenopausal women should be recommended. This possible effect has not been specifically investigated in clinical studies; therefore, the frequency of this occurrence is not known.

Although hormonal imbalance has been seen in preclinical studies [see Nonclinical Toxicology (13.1)], the clinical significance of this finding is not known. If unexpected menstrual dysfunction occurs, the benefits of continued therapy with AVANDIA should be reviewed.

6 ADVERSE REACTIONS

6.1 Clinical Trial Experience

Adult

In clinical trials, approximately 9,900 patients with type 2 diabetes have been treated with AVANDIA.

Short-Term Trials of AVANDIA as Monotherapy and in Combination With Other Hypoglycemic Agents

The incidence and types of adverse events reported in short-term clinical trials of AVANDIA as monotherapy are shown in Table 4.

Table 4. Adverse Events (≥5% in Any Treatment Group) Reported by Patients in Short-Term* Double-Blind Clinical Trials With AVANDIA as Monotherapy
Preferred Term | AVANDIA Monotherapy N = 2,526 % | Placebo N = 601 % | Metformin N = 225 % | Sulfonylureas† N = 626 %
Upper respiratory tract infection | 9.9 | 8.7 | 8.9 | 7.3
Injury | 7.6 | 43.3 | 7.6 | 6.1
Headache | 5.9 | 5.0 | 8.9 | 5.4
Back pain | 4.0 | 3.8 | 4.0 | 5.0
Hyperglycemia | 3.9 | 5.7 | 4.4 | 8.1
Fatigue | 3.6 | 5.0 | 4.0 | 1.9
Sinusitis | 3.2 | 4.5 | 5.3 | 3.0
Diarrhea | 2.3 | 3.3 | 15.6 | 3.0
Hypoglycemia | 0.6 | 0.2 | 1.3 | 5.9

* Short-term trials ranged from 8 weeks to 1 year.
† Includes patients receiving glyburide (N = 514), gliclazide (N = 91), or glipizide (N = 21).

Overall, the types of adverse reactions without regard to causality reported when AVANDIA was used in combination with a sulfonylurea or metformin were similar to those during monotherapy with AVANDIA.

Events of anemia and edema tended to be reported more frequently at higher doses, and were generally mild to moderate in severity and usually did not require discontinuation of treatment with AVANDIA.

In double-blind studies, anemia was reported in 1.9% of patients receiving AVANDIA as monotherapy compared to 0.7% on placebo, 0.6% on sulfonylureas, and 2.2% on metformin. Reports of anemia were greater in patients treated with a combination of AVANDIA and metformin (7.1%) and with a combination of AVANDIA and a sulfonylurea plus metformin (6.7%) compared to monotherapy with AVANDIA or in combination with a sulfonylurea (2.3%). Lower pre-treatment hemoglobin/hematocrit levels in patients enrolled in the metformin combination clinical trials may have contributed to the higher reporting rate of anemia in these studies [see Adverse Reactions (6.2)].

In clinical trials, edema was reported in 4.8% of patients receiving AVANDIA as monotherapy compared to 1.3% on placebo, 1.0% on sulfonylureas, and 2.2% on metformin. The reporting rate of edema was higher for AVANDIA 8 mg in sulfonylurea combinations (12.4%) compared to other combinations, with the exception of insulin. Edema was reported in 14.7% of patients receiving AVANDIA in the insulin combination trials compared to 5.4% on insulin alone. Reports of new onset or exacerbation of congestive heart failure occurred at rates of 1% for insulin alone, and 2% (4 mg) and 3% (8 mg) for insulin in combination with AVANDIA [see Boxed Warning and Warnings and Precautions (5.3)].

In controlled combination therapy studies with sulfonylureas, mild to moderate hypoglycemic symptoms, which appear to be dose related, were reported. Few patients were withdrawn for hypoglycemia (less than 1%) and few episodes of hypoglycemia were considered to be severe (less than 1%). Hypoglycemia was the most frequently reported adverse event in the fixed-dose insulin combination trials, although few patients withdrew for hypoglycemia (4 of 408 for AVANDIA plus insulin and 1 of 203 for insulin alone). Rates of hypoglycemia, confirmed by capillary blood glucose concentration less than or equal to 50 mg/dL, were 6% for insulin alone and 12% (4 mg) and 14% (8 mg) for insulin in combination with AVANDIA. [See Warnings and Precautions (5.10).]

Long-Term Trial of AVANDIA as Monotherapy

A 4- to 6-year study (ADOPT) compared the use of AVANDIA (n = 1,456), glyburide (n = 1,441), and metformin (n = 1,454) as monotherapy in patients recently diagnosed with type 2 diabetes who were not previously treated with antidiabetic medication. Table 5 presents adverse reactions without regard to causality; rates are expressed per 100 patient-years (PY) exposure to account for the differences in exposure to study medication across the 3 treatment groups.

In ADOPT, fractures were reported in a greater number of women treated with AVANDIA (9.3%, 2.7/100 patient-years) compared to glyburide (3.5%, 1.3/100 patient-years) or metformin (5.1%, 1.5/100 patient-years). The majority of the fractures in the women who received rosiglitazone were reported in the upper arm, hand, and foot. [See Warnings and Precautions (5.7).] The observed incidence of fractures for male patients was similar among the 3 treatment groups.

Table 5. On-Therapy Adverse Events (Greater Than or Equal To 5 Events/100 Patient-Years [PY]) in Any Treatment Group Reported in a 4- to 6-Year Clinical Trial of AVANDIA as Monotherapy (ADOPT)
 | AVANDIA | Glyburide | Metformin
 | N = 1,456 | N = 1,441 | N = 1,454
 | PY = 4,954 | PY = 4,244 | PY = 4,906
Nasopharyngitis | 6.3 | 6.9 | 6.6
Back pain | 5.1 | 4.9 | 5.3
Arthralgia | 5.0 | 4.8 | 4.2
Hypertension | 4.4 | 6.0 | 6.1
Upper respiratory tract infection | 4.3 | 5.0 | 4.7
Hypoglycemia | 2.9 | 13.0 | 3.4
Diarrhea | 2.5 | 3.2 | 6.8

Pediatric

AVANDIA has been evaluated for safety in a single, active-controlled trial of pediatric patients with type 2 diabetes in which 99 were treated with AVANDIA and 101 were treated with metformin. The most common adverse reactions (greater than 10%) without regard to causality for either AVANDIA or metformin were headache (17% versus 14%), nausea (4% versus 11%), nasopharyngitis (3% versus 12%), and diarrhea (1% versus 13%). In this study, one case of diabetic ketoacidosis was reported in the metformin group. In addition, there were 3 patients in the rosiglitazone group who had FPG of ∼300 mg/dL, 2+ ketonuria, and an elevated anion gap.

6.2 Laboratory Abnormalities

Hematologic

Decreases in mean hemoglobin and hematocrit occurred in a dose-related fashion in adult patients treated with AVANDIA (mean decreases in individual studies as much as 1.0 g/dL hemoglobin and as much as 3.3% hematocrit). The changes occurred primarily during the first 3 months following initiation of therapy with AVANDIA or following a dose increase in AVANDIA. The time course and magnitude of decreases were similar in patients treated with a combination of AVANDIA and other hypoglycemic agents or monotherapy with AVANDIA. Pre-treatment levels of hemoglobin and hematocrit were lower in patients in metformin combination studies and may have contributed to the higher reporting rate of anemia. In a single study in pediatric patients, decreases in hemoglobin and hematocrit (mean decreases of 0.29 g/dL and 0.95%, respectively) were reported. Small decreases in hemoglobin and hematocrit have also been reported in pediatric patients treated with AVANDIA. White blood cell counts also decreased slightly in adult patients treated with AVANDIA. Decreases in hematologic parameters may be related to increased plasma volume observed with treatment with AVANDIA.

Lipids

Changes in serum lipids have been observed following treatment with AVANDIA in adults [see Clinical Pharmacology (12.2)]. Small changes in serum lipid parameters were reported in children treated with AVANDIA for 24 weeks.

Serum Transaminase Levels

In pre-approval clinical studies in 4,598 patients treated with AVANDIA (3,600 patient-years of exposure) and in a long-term 4- to 6-year study in 1,456 patients treated with AVANDIA (4,954 patient-years exposure), there was no evidence of drug-induced hepatotoxicity.

In pre-approval controlled trials, 0.2% of patients treated with AVANDIA had elevations in ALT >3X the upper limit of normal compared to 0.2% on placebo and 0.5% on active comparators. The ALT elevations in patients treated with AVANDIA were reversible. Hyperbilirubinemia was found in 0.3% of patients treated with AVANDIA compared with 0.9% treated with placebo and 1% in patients treated with active comparators. In pre-approval clinical trials, there were no cases of idiosyncratic drug reactions leading to hepatic failure. [See Warnings and Precautions (5.6).]

In the 4- to 6-year ADOPT trial, patients treated with AVANDIA (4,954 patient-years exposure), glyburide (4,244 patient-years exposure), or metformin (4,906 patient-years exposure), as monotherapy, had the same rate of ALT increase to greater than 3X upper limit of normal (0.3 per 100 patient-years exposure).

6.3 Postmarketing Experience

In addition to adverse reactions reported from clinical trials, the events described below have been identified during post-approval use of AVANDIA. Because these events are reported voluntarily from a population of unknown size, it is not possible to reliably estimate their frequency or to always establish a causal relationship to drug exposure.

In patients receiving thiazolidinedione therapy, serious adverse events with or without a fatal outcome, potentially related to volume expansion (e.g., congestive heart failure, pulmonary edema, and pleural effusions) have been reported [see Boxed Warning and Warnings and Precautions (5.1)].

There are postmarketing reports with AVANDIA of hepatitis, hepatic enzyme elevations to 3 or more times the upper limit of normal, and hepatic failure with and without fatal outcome, although causality has not been established.

There are postmarketing reports with AVANDIA of rash, pruritus, urticaria, angioedema, anaphylactic reaction, Stevens-Johnson syndrome, and new onset or worsening diabetic macular edema with decreased visual acuity [see Warnings and Precautions (5.7)].

7 DRUG INTERACTIONS

7.1 CYP2C8 Inhibitors and Inducers

An inhibitor of CYP2C8 (e.g., gemfibrozil) may increase the AUC of rosiglitazone and an inducer of CYP2C8 (e.g., rifampin) may decrease the AUC of rosiglitazone. Therefore, if an inhibitor or an inducer of CYP2C8 is started or stopped during treatment with rosiglitazone, changes in diabetes treatment may be needed based upon clinical response. [See Clinical Pharmacology (12.4).]

8 USE IN SPECIFIC POPULATIONS

8.1 Pregnancy

Pregnancy Category C.

All pregnancies have a background risk of birth defects, loss, or other adverse outcome regardless of drug exposure. This background risk is increased in pregnancies complicated by hyperglycemia and may be decreased with good metabolic control. It is essential for patients with diabetes or history of gestational diabetes to maintain good metabolic control before conception and throughout pregnancy. Careful monitoring of glucose control is essential in such patients. Most experts recommend that insulin monotherapy be used during pregnancy to maintain blood glucose levels as close to normal as possible.

Human Data

Rosiglitazone has been reported to cross the human placenta and be detectable in fetal tissue. The clinical significance of these findings is unknown. There are no adequate and well-controlled studies in pregnant women. AVANDIA should not be used during pregnancy.

Animal Studies

There was no effect on implantation or the embryo with rosiglitazone treatment during early pregnancy in rats, but treatment during mid-late gestation was associated with fetal death and growth retardation in both rats and rabbits. Teratogenicity was not observed at doses up to 3 mg/kg in rats and 100 mg/kg in rabbits (approximately 20 and 75 times human AUC at the maximum recommended human daily dose, respectively). Rosiglitazone caused placental pathology in rats (3 mg/kg/day). Treatment of rats during gestation through lactation reduced litter size, neonatal viability, and postnatal growth, with growth retardation reversible after puberty. For effects on the placenta, embryo/fetus, and offspring, the no-effect dose was 0.2 mg/kg/day in rats and 15 mg/kg/day in rabbits. These no-effect levels are approximately 4 times human AUC at the maximum recommended human daily dose. Rosiglitazone reduced the number of uterine implantations and live offspring when juvenile female rats were treated at 40 mg/kg/day from 27 days of age through to sexual maturity (approximately 68 times human AUC at the maximum recommended daily dose). The no-effect level was 2 mg/kg/day (approximately 4 times human AUC at the maximum recommended daily dose). There was no effect on pre- or post-natal survival or growth.

8.2 Labor and Delivery

The effect of rosiglitazone on labor and delivery in humans is not known.

8.3 Nursing Mothers

Drug-related material was detected in milk from lactating rats. It is not known whether AVANDIA is excreted in human milk. Because many drugs are excreted in human milk, AVANDIA should not be administered to a nursing woman.

8.4 Pediatric Use

After placebo run-in including diet counseling, children with type 2 diabetes mellitus, aged 10 to 17 years and with a baseline mean body mass index (BMI) of 33 kg/m^2, were randomized to treatment with 2 mg twice daily of AVANDIA (n = 99) or 500 mg twice daily of metformin (n = 101) in a 24-week, double-blind clinical trial. As expected, FPG decreased in patients naïve to diabetes medication (n = 104) and increased in patients withdrawn from prior medication (usually metformin) (n = 90) during the run-in period. After at least 8 weeks of treatment, 49% of patients treated with AVANDIA and 55% of metformin-treated patients had their dose doubled if FPG >126 mg/dL. For the overall intent-to-treat population, at week 24, the mean change from baseline in HbA1c was -0.14% with AVANDIA and -0.49% with metformin. There was an insufficient number of patients in this study to establish statistically whether these observed mean treatment effects were similar or different. Treatment effects differed for patients naïve to therapy with antidiabetic drugs and for patients previously treated with antidiabetic therapy (Table 6).

Table 6. Week 24 FPG and HbA1c Change From Baseline Last-Observation-Carried Forward in Children With Baseline HbA1c >6.5%
 | Naïve | Patients | Previously- | Treated Patients
 | Metformin N = 40 | Rosiglitazone N = 45 | Metformin N - 43 | Rosiglitazone N = 32
FPG (mg/dL)
Baseline (mean) | 170 | 165 | 221 | 205
Change from baseline (mean) | -21 | -11 | -33 | -5
Adjusted treatment difference* (rosiglitazone-metformin)† (95% CI) |  | 8 (-15, 30) |  | 21 (-9, 51)
% of patients with ≥30 mg/dL decrease from baseline | 43% | 27% | 44% | 28%
HbAlc (%)
Baseline (mean) | 8.3 | 8.2 | 8.8 | 8.5
Change from baseline (mean) | -0.7 | -0.5 | -0.4 | 0.1
Adjusted treatment difference* (rosiglitazone-metformin)† (95% CI) |  | 0.2 (-0.6, 0.9) |  | 0.5 (-0.2, 1.3)
% of patients with ≥0.7% decrease from baseline | 63% | 52% | 54% | 31%

* Change from baseline means are least squares means adjusting for baseline HbA1c, gender, and region.

† Positive values for the difference favor metformin.

Treatment differences depended on baseline BMI or weight such that the effects of AVANDIA and metformin appeared more closely comparable among heavier patients. The median weight gain was 2.8 kg with rosiglitazone and 0.2 kg with metformin [see Warnings and Precautions (5.4)]. Fifty-four percent of patients treated with rosiglitazone and 32% of patients treated with metformin gained ≥2 kg, and 33% of patients treated with rosiglitazone and 7% of patients treated with metformin gained ≥5 kg on study.

Adverse events observed in this study are described in Adverse Reactions (6.1).

Figure 3. Mean HbA1c Over Time in a 24-Week Study of AVANDIA and Metformin in Pediatric Patients — Drug-Naïve Subgroup

8.5 Geriatric Use

Results of the population pharmacokinetic analysis showed that age does not significantly affect the pharmacokinetics of rosiglitazone [see Clinical Pharmacology (12.3)]. Therefore, no dosage adjustments are required for the elderly. In controlled clinical trials, no overall differences in safety and effectiveness between older (greater than or equal to 65 years) and younger (less than 65 years) patients were observed.

10 OVERDOSAGE

Limited data are available with regard to overdosage in humans. In clinical studies in volunteers, AVANDIA has been administered at single oral doses of up to 20 mg and was well-tolerated. In the event of an overdose, appropriate supportive treatment should be initiated as dictated by the patient’s clinical status.

11 DESCRIPTION

AVANDIA (rosiglitazone maleate) is an oral antidiabetic agent which acts primarily by increasing insulin sensitivity. AVANDIA improves glycemic control while reducing circulating insulin levels.

Rosiglitazone maleate is not chemically or functionally related to the sulfonylureas, the biguanides, or the alpha-glucosidase inhibitors.

Chemically, rosiglitazone maleate is (±)-5-[[4-[2-(methyl-2-pyridinylamino)ethoxy]phenyl]methyl]-2,4-thiazolidinedione, (Z)-2-butenedioate (1:1) with a molecular weight of 473.52 (357.44 free base). The molecule has a single chiral center and is present as a racemate. Due to rapid interconversion, the enantiomers are functionally indistinguishable. The structural formula of rosiglitazone maleate is:

The molecular formula is C18H19N3O3S•C4H4O4. Rosiglitazone maleate is a white to off-white solid with a melting point range of 122° to 123°C. The pKa values of rosiglitazone maleate are 6.8 and 6.1. It is readily soluble in ethanol and a buffered aqueous solution with pH of 2.3; solubility decreases with increasing pH in the physiological range.

Each pentagonal film-coated TILTAB tablet contains rosiglitazone maleate equivalent to rosiglitazone, 2 mg, 4 mg, or 8 mg, for oral administration. Inactive ingredients are: Hypromellose 2910, lactose monohydrate, magnesium stearate, microcrystalline cellulose, polyethylene glycol 3000, sodium starch glycolate, titanium dioxide, triacetin, and 1 or more of the following: Synthetic red and yellow iron oxides and talc.

12 CLINICAL PHARMACOLOGY

12.1 Mechanism of Action

Rosiglitazone, a member of the thiazolidinedione class of antidiabetic agents, improves glycemic control by improving insulin sensitivity. Rosiglitazone is a highly selective and potent agonist for the peroxisome proliferator-activated receptor-gamma (PPARγ). In humans, PPAR receptors are found in key target tissues for insulin action such as adipose tissue, skeletal muscle, and liver. Activation of PPARγ nuclear receptors regulates the transcription of insulin-responsive genes involved in the control of glucose production, transport, and utilization. In addition, PPARγ-responsive genes also participate in the regulation of fatty acid metabolism.

Insulin resistance is a common feature characterizing the pathogenesis of type 2 diabetes. The antidiabetic activity of rosiglitazone has been demonstrated in animal models of type 2 diabetes in which hyperglycemia and/or impaired glucose tolerance is a consequence of insulin resistance in target tissues. Rosiglitazone reduces blood glucose concentrations and reduces hyperinsulinemia in the ob/ob obese mouse, db/db diabetic mouse, and fa/fa fatty Zucker rat.

In animal models, the antidiabetic activity of rosiglitazone was shown to be mediated by increased sensitivity to insulin’s action in the liver, muscle, and adipose tissues. Pharmacological studies in animal models indicate that rosiglitazone inhibits hepatic gluconeogenesis. The expression of the insulin-regulated glucose transporter GLUT-4 was increased in adipose tissue. Rosiglitazone did not induce hypoglycemia in animal models of type 2 diabetes and/or impaired glucose tolerance.

12.2 Pharmacodynamics

Patients with lipid abnormalities were not excluded from clinical trials of AVANDIA. In all 26-week controlled trials, across the recommended dose range, AVANDIA as monotherapy was associated with increases in total cholesterol, LDL, and HDL and decreases in free fatty acids. These changes were statistically significantly different from placebo or glyburide controls (Table 7).

Increases in LDL occurred primarily during the first 1 to 2 months of therapy with AVANDIA and LDL levels remained elevated above baseline throughout the trials. In contrast, HDL continued to rise over time. As a result, the LDL/HDL ratio peaked after 2 months of therapy and then appeared to decrease over time. Because of the temporal nature of lipid changes, the 52-week glyburide-controlled study is most pertinent to assess long-term effects on lipids. At baseline, week 26, and week 52, mean LDL/HDL ratios were 3.1, 3.2, and 3.0, respectively, for AVANDIA 4 mg twice daily. The corresponding values for glyburide were 3.2, 3.1, and 2.9. The differences in change from baseline between AVANDIA and glyburide at week 52 were statistically significant.

The pattern of LDL and HDL changes following therapy with AVANDIA in combination with other hypoglycemic agents were generally similar to those seen with AVANDIA in monotherapy.

The changes in triglycerides during therapy with AVANDIA were variable and were generally not statistically different from placebo or glyburide controls.

Table 7. Summary of Mean Lipid Changes in 26-Week Placebo-Controlled and 52-Week Glyburide-Controlled Monotherapy Studies
 | Placebo- | Controlled Week 26 | Studies | Glyburide- Study and | Controlled Week 26 Week 52
 | Placebo | AVANDIA | AVANDIA | Glyburide | Titration | AVANDIA | 8 mg
 |  | 4mg daily* | 8 mg daily* | Wk 26 | Wk 52 | Wk 26 | Wk 52
Free Fatty acids
N | 207 | 428 | 436 | 181 | 168 | 166 | 145
Baselline (mean) | 18.1 | 17.5 | 17.9 | 26.4 | 26.4 | 26.9 | 26.6
% Change from baseline (mean) | +0.2% | -7.8% | -14.7% | -2.4% | -4.7% | -20.8% | -21.5%
LDL
N | 190 | 400 | 374 | 175 | 160 | 161 | 133
Baselline (mean) | 123.7 | 126.8 | 125.3 | 142.7 | 141.9 | 142.1 | 142.1
% Change from baseline (mean) | +4.8% | +14.1% | +18.6% | -0.9% | -0.5% | +11.9% | +12.1%
HDL
N | 208 | 429 | 436 | 184 | 170 | 170 | 145
Baselline (mean) | 44.1 | 44.4 | 43.0 | 47.2 | 47.7 | 48.4 | 48.3
% Change from baseline (mean) | +8.0% | +11.4% | +14.2% | +4.3% | +8.7% | +14.0% | +18.5%

* Once daily and twice daily dosing groups were combined.
12.3 Pharmacokinetics

Maximum plasma concentration (Cmax) and the area under the curve (AUC) of rosiglitazone increase in a dose-proportional manner over the therapeutic dose range (Table 8). The elimination half-life is 3 to 4 hours and is independent of dose.

Table 8. Mean (SD) Pharmacokinetic Parameters for Rosiglitazone Following Single Oral Doses (N = 32)
Parameter | 1 mg Fasting | 2 mg Fasting | 8 mg Fasting | 8 mg Fed
AUC0-inf; [ng•hr/mL] | 358 (112) | 733 (184) | 2,971 (730) | 2,890 (795)
Cmax; [ng/mL] | 76 (13) | 156 (42) | 598 (117) | 432 (92)
Half-life; [hr] | 3.16 (0.72) | 3.15 (0.39) | 3.37 (0.63) | 3.59 (0.70)
CL/F*; [L/hr] | 3.03 (0.87) | 2.89 (0.71) | 2.85 (0.69) | 2.97 (0.81)

* CL/F = Oral clearance.

Absorption

The absolute bioavailability of rosiglitazone is 99%. Peak plasma concentrations are observed about 1 hour after dosing. Administration of rosiglitazone with food resulted in no change in overall exposure (AUC), but there was an approximately 28% decrease in Cmax and a delay in Tmax (1.75 hours). These changes are not likely to be clinically significant; therefore, AVANDIA may be administered with or without food.

Distribution

The mean (CV%) oral volume of distribution (Vss/F) of rosiglitazone is approximately 17.6 (30%) liters, based on a population pharmacokinetic analysis. Rosiglitazone is approximately 99.8% bound to plasma proteins, primarily albumin.

Metabolism

Rosiglitazone is extensively metabolized with no unchanged drug excreted in the urine. The major routes of metabolism were N-demethylation and hydroxylation, followed by conjugation with sulfate and glucuronic acid. All the circulating metabolites are considerably less potent than parent and, therefore, are not expected to contribute to the insulin-sensitizing activity of rosiglitazone.

In vitro data demonstrate that rosiglitazone is predominantly metabolized by Cytochrome P450 (CYP) isoenzyme 2C8, with CYP2C9 contributing as a minor pathway.

Excretion

Following oral or intravenous administration of [^14C]rosiglitazone maleate, approximately 64% and 23% of the dose was eliminated in the urine and in the feces, respectively. The plasma half-life of [^14C]related material ranged from 103 to 158 hours.

Population Pharmacokinetics in Patients With Type 2 Diabetes

Population pharmacokinetic analyses from 3 large clinical trials including 642 men and 405 women with type 2 diabetes (aged 35 to 80 years) showed that the pharmacokinetics of rosiglitazone are not influenced by age, race, smoking, or alcohol consumption. Both oral clearance (CL/F) and oral steady-state volume of distribution (Vss/F) were shown to increase with increases in body weight. Over the weight range observed in these analyses (50 to 150 kg), the range of predicted CL/F and Vss/F values varied by less than 1.7-fold and less than 2.3-fold, respectively. Additionally, rosiglitazone CL/F was shown to be influenced by both weight and gender, being lower (about 15%) in female patients.

Special Populations

Geriatric

Results of the population pharmacokinetic analysis (n = 716 less than 65 years; n = 331 greater than or equal to 65 years) showed that age does not significantly affect the pharmacokinetics of rosiglitazone.

Gender

Results of the population pharmacokinetics analysis showed that the mean oral clearance of rosiglitazone in female patients (n = 405) was approximately 6% lower compared to male patients of the same body weight (n = 642).

As monotherapy and in combination with metformin, AVANDIA improved glycemic control in both males and females. In metformin combination studies, efficacy was demonstrated with no gender differences in glycemic response.

In monotherapy studies, a greater therapeutic response was observed in females; however, in more obese patients, gender differences were less evident. For a given body mass index (BMI), females tend to have a greater fat mass than males. Since the molecular target PPARγ is expressed in adipose tissues, this differentiating characteristic may account, at least in part, for the greater response to AVANDIA in females. Since therapy should be individualized, no dose adjustments are necessary based on gender alone.

Hepatic Impairment

Unbound oral clearance of rosiglitazone was significantly lower in patients with moderate to severe liver disease (Child-Pugh Class B/C) compared to healthy subjects. As a result, unbound Cmax and AUC0-inf were increased 2- and 3-fold, respectively. Elimination half-life for rosiglitazone was about 2 hours longer in patients with liver disease, compared to healthy subjects.

Therapy with AVANDIA should not be initiated if the patient exhibits clinical evidence of active liver disease or increased serum transaminase levels (ALT greater than 2.5X upper limit of normal) at baseline [see Warnings and Precautions (5.6)].

Pediatric

Pharmacokinetic parameters of rosiglitazone in pediatric patients were established using a population pharmacokinetic analysis with sparse data from 96 pediatric patients in a single pediatric clinical trial including 33 males and 63 females with ages ranging from 10 to 17 years (weights ranging from 35 to 178.3 kg). Population mean CL/F and V/F of rosiglitazone were 3.15 L/hr and 13.5 L, respectively. These estimates of CL/F and V/F were consistent with the typical parameter estimates from a prior adult population analysis.

Renal Impairment

There are no clinically relevant differences in the pharmacokinetics of rosiglitazone in patients with mild to severe renal impairment or in hemodialysis-dependent patients compared to subjects with normal renal function. No dosage adjustment is therefore required in such patients receiving AVANDIA. Since metformin is contraindicated in patients with renal impairment, coadministration of metformin with AVANDIA is contraindicated in these patients.

Race

Results of a population pharmacokinetic analysis including subjects of Caucasian, black, and other ethnic origins indicate that race has no influence on the pharmacokinetics of rosiglitazone.

12.4 Drug-Drug Interactions

Drugs That Inhibit, Induce, or are Metabolized by Cytochrome P450

In vitro drug metabolism studies suggest that rosiglitazone does not inhibit any of the major P450 enzymes at clinically relevant concentrations. In vitro data demonstrate that rosiglitazone is predominantly metabolized by CYP2C8, and to a lesser extent, 2C9. AVANDIA (4 mg twice daily) was shown to have no clinically relevant effect on the pharmacokinetics of nifedipine and oral contraceptives (ethinyl estradiol and norethindrone), which are predominantly metabolized by CYP3A4.

Gemfibrozil

Concomitant administration of gemfibrozil (600 mg twice daily), an inhibitor of CYP2C8, and rosiglitazone (4 mg once daily) for 7 days increased rosiglitazone AUC by 127%, compared to the administration of rosiglitazone (4 mg once daily) alone. Given the potential for dose-related adverse events with rosiglitazone, a decrease in the dose of rosiglitazone may be needed when gemfibrozil is introduced [see Drug Interactions (7.1)].

Rifampin

Rifampin administration (600 mg once a day), an inducer of CYP2C8, for 6 days is reported to decrease rosiglitazone AUC by 66%, compared to the administration of rosiglitazone (8 mg) alone [see Drug Interactions (7.1)].^4

Glyburide

AVANDIA (2 mg twice daily) taken concomitantly with glyburide (3.75 to 10 mg/day) for 7 days did not alter the mean steady-state 24-hour plasma glucose concentrations in diabetic patients stabilized on glyburide therapy. Repeat doses of AVANDIA (8 mg once daily) for 8 days in healthy adult Caucasian subjects caused a decrease in glyburide AUC and Cmax of approximately 30%. In Japanese subjects, glyburide AUC and Cmax slightly increased following coadministration of AVANDIA.

Glimepiride

Single oral doses of glimepiride in 14 healthy adult subjects had no clinically significant effect on the steady-state pharmacokinetics of AVANDIA. No clinically significant reductions in glimepiride AUC and Cmax were observed after repeat doses of AVANDIA (8 mg once daily) for 8 days in healthy adult subjects.

Metformin

Concurrent administration of AVANDIA (2 mg twice daily) and metformin (500 mg twice daily) in healthy volunteers for 4 days had no effect on the steady-state pharmacokinetics of either metformin or rosiglitazone.

Acarbose

Coadministration of acarbose (100 mg three times daily) for 7 days in healthy volunteers had no clinically relevant effect on the pharmacokinetics of a single oral dose of AVANDIA.

Digoxin

Repeat oral dosing of AVANDIA (8 mg once daily) for 14 days did not alter the steady-state pharmacokinetics of digoxin (0.375 mg once daily) in healthy volunteers.

Warfarin

Repeat dosing with AVANDIA had no clinically relevant effect on the steady-state pharmacokinetics of warfarin enantiomers.

Ethanol

A single administration of a moderate amount of alcohol did not increase the risk of acute hypoglycemia in type 2 diabetes mellitus patients treated with AVANDIA.

Ranitidine

Pretreatment with ranitidine (150 mg twice daily for 4 days) did not alter the pharmacokinetics of either single oral or intravenous doses of rosiglitazone in healthy volunteers. These results suggest that the absorption of oral rosiglitazone is not altered in conditions accompanied by increases in gastrointestinal pH.

13 NONCLINICAL TOXICOLOGY

13.1 Carcinogenesis, Mutagenesis, Impairment of Fertility

Carcinogenesis

A 2-year carcinogenicity study was conducted in Charles River CD-1 mice at doses of 0.4, 1.5, and 6 mg/kg/day in the diet (highest dose equivalent to approximately 12 times human AUC at the maximum recommended human daily dose). Sprague-Dawley rats were dosed for 2 years by oral gavage at doses of 0.05, 0.3, and 2 mg/kg/day (highest dose equivalent to approximately 10 and 20 times human AUC at the maximum recommended human daily dose for male and female rats, respectively).

Rosiglitazone was not carcinogenic in the mouse. There was an increase in incidence of adipose hyperplasia in the mouse at doses ≥1.5 mg/kg/day (approximately 2 times human AUC at the maximum recommended human daily dose). In rats, there was a significant increase in the incidence of benign adipose tissue tumors (lipomas) at doses ≥0.3 mg/kg/day (approximately 2 times human AUC at the maximum recommended human daily dose). These proliferative changes in both species are considered due to the persistent pharmacological overstimulation of adipose tissue.

Mutagenesis

Rosiglitazone was not mutagenic or clastogenic in the in vitro bacterial assays for gene mutation, the in vitro chromosome aberration test in human lymphocytes, the in vivo mouse micronucleus test, and the in vivo/in vitro rat UDS assay. There was a small (about 2-fold) increase in mutation in the in vitro mouse lymphoma assay in the presence of metabolic activation.

Impairment of Fertility

Rosiglitazone had no effects on mating or fertility of male rats given up to 40 mg/kg/day (approximately 116 times human AUC at the maximum recommended human daily dose). Rosiglitazone altered estrous cyclicity (2 mg/kg/day) and reduced fertility (40 mg/kg/day) of female rats in association with lower plasma levels of progesterone and estradiol (approximately 20 and 200 times human AUC at the maximum recommended human daily dose, respectively). No such effects were noted at 0.2 mg/kg/day (approximately 3 times human AUC at the maximum recommended human daily dose). In juvenile rats dosed from 27 days of age through to sexual maturity (at up to 40 mg/kg/day), there was no effect on male reproductive performance, or on estrous cyclicity, mating performance or pregnancy incidence in females (approximately 68 times human AUC at the maximum recommended human daily dose). In monkeys, rosiglitazone (0.6 and 4.6 mg/kg/day; approximately 3 and 15 times human AUC at the maximum recommended human daily dose, respectively) diminished the follicular phase rise in serum estradiol with consequential reduction in the luteinizing hormone surge, lower luteal phase progesterone levels, and amenorrhea. The mechanism for these effects appears to be direct inhibition of ovarian steroidogenesis.

13.2 Animal Toxicology

Heart weights were increased in mice (3 mg/kg/day), rats (5 mg/kg/day), and dogs (2 mg/kg/day) with rosiglitazone treatments (approximately 5, 22, and 2 times human AUC at the maximum recommended human daily dose, respectively). Effects in juvenile rats were consistent with those seen in adults. Morphometric measurement indicated that there was hypertrophy in cardiac ventricular tissues, which may be due to increased heart work as a result of plasma volume expansion.

14 CLINICAL STUDIES

14.1 Monotherapy

In clinical studies, treatment with AVANDIA resulted in an improvement in glycemic control, as measured by FPG and HbA1c, with a concurrent reduction in insulin and C-peptide. Postprandial glucose and insulin were also reduced. This is consistent with the mechanism of action of AVANDIA as an insulin sensitizer.

The maximum recommended daily dose is 8 mg. Dose-ranging studies suggested that no additional benefit was obtained with a total daily dose of 12 mg.

Short-Term Clinical Studies

A total of 2,315 patients with type 2 diabetes, previously treated with diet alone or antidiabetic medication(s), were treated with AVANDIA as monotherapy in 6 double-blind studies, which included two 26-week placebo-controlled studies, one 52-week glyburide-controlled study, and 3 placebo-controlled dose-ranging studies of 8 to 12 weeks duration. Previous antidiabetic medication(s) were withdrawn and patients entered a 2 to 4 week placebo run-in period prior to randomization.

Two 26-week, double-blind, placebo-controlled trials, in patients with type 2 diabetes (n = 1,401) with inadequate glycemic control (mean baseline FPG approximately 228 mg/dL [101 to 425 mg/dL] and mean baseline HbA1c 8.9% [5.2% to 16.2%]), were conducted. Treatment with AVANDIA produced statistically significant improvements in FPG and HbA1c compared to baseline and relative to placebo. Data from one of these studies are summarized in Table 9.

Table 9. Glycemic Parameters in a 26-Week Placebo-Controlled Trial
 | Placebo | AVANDIA | AVANDIA | AVANDIA | AVANDIA
 |  | 4 mg once daily | 2 mg twice daily | 8 mg once daily | 4 mg twice daily
 | N = 173 | N = 180 | N = 186 | N = 181 | N = 187
FPG (mg/dL)
Baseline (mean) | 225 | 229 | 225 | 228 | 228
Change from baseline (mean) | 8 | -25 | -35 | -42 | -55
Difference from placebo (adjusted mean) | -- | -31* | -43* | -49* | -62*
% of patients with ≥30 mg/dL decrease from baseline | 19% | 45% | 54% | 58% | 70%
HbAlc (%)
Baseline (mean) | 8.9 | 8.9 | 8.9 | 8.9 | 9.0
Change from baseline (mean) | 0.8 | 0.0 | -0.1 | -0.3 | -0.7
Difference from placebo (adjusted mean) | -- | -0.8* | -0.9* | -1.1* | -1.5*
% of patients with ≥0.7% decrease from baseline | 9% | 28% | 29% | 39% | 54%

* p less than 0.0001 compared to placebo.

When administered at the same total daily dose, AVANDIA was generally more effective in reducing FPG and HbA1c when administered in divided doses twice daily compared to once daily doses. However, for HbA1c, the difference between the 4 mg once daily and 2 mg twice daily doses was not statistically significant.

Long-Term Clinical Studies

Long-term maintenance of effect was evaluated in a 52-week, double-blind, glyburide-controlled trial in patients with type 2 diabetes. Patients were randomized to treatment with AVANDIA 2 mg twice daily (N = 195) or AVANDIA 4 mg twice daily (N = 189) or glyburide (N = 202) for 52 weeks. Patients receiving glyburide were given an initial dosage of either 2.5 mg/day or 5.0 mg/day. The dosage was then titrated in 2.5 mg/day increments over the next 12 weeks, to a maximum dosage of 15.0 mg/day in order to optimize glycemic control. Thereafter, the glyburide dose was kept constant.

The median titrated dose of glyburide was 7.5 mg. All treatments resulted in a statistically significant improvement in glycemic control from baseline (Figure 4 and Figure 5). At the end of week 52, the reduction from baseline in FPG and HbA1c was -40.8 mg/dL and -0.53% with AVANDIA 4 mg twice daily; -25.4 mg/dL and -0.27% with AVANDIA 2 mg twice daily; and -30.0 mg/dL and -0.72% with glyburide. For HbA1c, the difference between AVANDIA 4 mg twice daily and glyburide was not statistically significant at week 52. The initial fall in FPG with glyburide was greater than with AVANDIA; however, this effect was less durable over time. The improvement in glycemic control seen with AVANDIA 4 mg twice daily at week 26 was maintained through week 52 of the study.
Figure 4. Mean FPG Over Time in a 52-Week Glyburide-Controlled Study

Figure 5. Mean HbA1c Over Time in a 52-Week Glyburide-Controlled Study

Hypoglycemia was reported in 12.1% of glyburide-treated patients versus 0.5% (2 mg twice daily) and 1.6% (4 mg twice daily) of patients treated with AVANDIA. The improvements in glycemic control were associated with a mean weight gain of 1.75 kg and 2.95 kg for patients treated with 2 mg and 4 mg twice daily of AVANDIA, respectively, versus 1.9 kg in glyburide-treated patients. In patients treated with AVANDIA, C-peptide, insulin, pro-insulin, and pro-insulin split products were significantly reduced in a dose-ordered fashion, compared to an increase in the glyburide-treated patients.

A Diabetes Outcome Progression Trial (ADOPT) was a multicenter, double-blind, controlled trial (N = 4,351) conducted over 4 to 6 years to compare the safety and efficacy of AVANDIA, metformin, and glyburide monotherapy in patients recently diagnosed with type 2 diabetes mellitus (≤3 years) inadequately controlled with diet and exercise. The mean age of patients in this trial was 57 years and the majority of patients (83%) had no known history of cardiovascular disease. The mean baseline FPG and HbA1c were 152 mg/dL and 7.4%, respectively. Patients were randomized to receive either AVANDIA 4 mg once daily, glyburide 2.5 mg once daily, or metformin 500 mg once daily, and doses were titrated to optimal glycemic control up to a maximum of 4 mg twice daily for AVANDIA, 7.5 mg twice daily for glyburide, and 1,000 mg twice daily for metformin. The primary efficacy outcome was time to consecutive FPG >180 mg/dL after at least 6 weeks of treatment at the maximum tolerated dose of study medication or time to inadequate glycemic control, as determined by an independent adjudication committee.

The cumulative incidence of the primary efficacy outcome at 5 years was 15% with AVANDIA, 21% with metformin, and 34% with glyburide (hazard ratio 0.68 [95% CI 0.55, 0.85] versus metformin, HR 0.37 [95% CI 0.30, 0.45] versus glyburide).

Cardiovascular and adverse event data (including effects on body weight and bone fracture) from ADOPT for AVANDIA, metformin, and glyburide are described in Warnings and Precautions (5.2, 5.5, and 5.8) and Adverse Reactions (6.1), respectively. As with all medications, efficacy results must be considered together with safety information to assess the potential benefit and risk for an individual patient.

14.2 Combination With Metformin or Sulfonylurea

The addition of AVANDIA to either metformin or sulfonylurea resulted in significant reductions in hyperglycemia compared to either of these agents alone. These results are consistent with an additive effect on glycemic control when AVANDIA is used as combination therapy.

Combination With Metformin

A total of 670 patients with type 2 diabetes participated in two 26-week, randomized, double-blind, placebo/active-controlled studies designed to assess the efficacy of AVANDIA in combination with metformin. AVANDIA, administered in either once daily or twice daily dosing regimens, was added to the therapy of patients who were inadequately controlled on a maximum dose (2.5 grams/day) of metformin.

In one study, patients inadequately controlled on 2.5 grams/day of metformin (mean baseline FPG 216 mg/dL and mean baseline HbA1c 8.8%) were randomized to receive 4 mg of AVANDIA once daily, 8 mg of AVANDIA once daily, or placebo in addition to metformin. A statistically significant improvement in FPG and HbA1c was observed in patients treated with the combinations of metformin and 4 mg of AVANDIA once daily and 8 mg of AVANDIA once daily, versus patients continued on metformin alone (Table 10).

Table 10. Glycemic Parameters in a 26-Week Combination Study of AVANDIA Plus Metformin
 | Metformin | AVANDIA | AVANDIA
 |  | 4 mg once daily + metformin | 8 mg once daily + metformin
 | N = 113 | N = 116 | N = 110
FPG (mg/dL)
Baseline (mean) | 214 | 215 | 220
Change from baseline (mean) | 6 | -33 | -48
Difference from metformin alone (adjusted mean) | -- | -40* | -53*
% of patients with ≥30 mg/dL decrease from baseline | 20% | 45% | 61%
HbAlc (%)
Baseline (mean) | 8.6 | 8.9 | 8.9
Change from baseline (mean) | 0.5 | -0.6 | -0.8
Difference from metformin alone (adjusted mean) | -- | -1.0* | -1.2*
% of patients with ≥0.7% decrease from baseline | 11% | 45% | 52%

* p less than 0.0001 compared to metformin.

In a second 26-week study, patients with type 2 diabetes inadequately controlled on 2.5 grams/day of metformin who were randomized to receive the combination of AVANDIA 4 mg twice daily and metformin (N = 105) showed a statistically significant improvement in glycemic control with a mean treatment effect for FPG of -56 mg/dL and a mean treatment effect for HbA1c of -0.8% over metformin alone. The combination of metformin and AVANDIA resulted in lower levels of FPG and HbA1c than either agent alone.

Patients who were inadequately controlled on a maximum dose (2.5 grams/day) of metformin and who were switched to monotherapy with AVANDIA demonstrated loss of glycemic control, as evidenced by increases in FPG and HbA1c. In this group, increases in LDL and VLDL were also seen.

Combination With a Sulfonylurea

A total of 3,457 patients with type 2 diabetes participated in ten 24- to 26-week randomized, double-blind, placebo/active-controlled studies and one 2-year double-blind, active-controlled study in elderly patients designed to assess the efficacy and safety of AVANDIA in combination with a sulfonylurea. AVANDIA 2 mg, 4 mg, or 8 mg daily was administered, either once daily (3 studies) or in divided doses twice daily (7 studies), to patients inadequately controlled on a submaximal or maximal dose of sulfonylurea.

In these studies, the combination of AVANDIA 4 mg or 8 mg daily (administered as single or twice daily divided doses) and a sulfonylurea significantly reduced FPG and HbA1c compared to placebo plus sulfonylurea or further up-titration of the sulfonylurea. Table 11 shows pooled data for 8 studies in which AVANDIA added to sulfonylurea was compared to placebo plus sulfonylurea.

Table 11. Glycemic Parameters in 24- to 26-Week Combination Studies of AVANDIA Plus Sulfonylurea
Twice Daily Divided Dosing (5 Studies) | Sulfonylurea | AVANDIA 2 mg twice daily + sulfonylurea | Sulfonylurea | AVANDIA 4 mg twice daily + sulfonylurea
 | N = 397 | N = 497 | N = 248 | N = 346
FPG (mg/dL)
Baseline (mean) | 204 | 198 | 188 | 187
Change from baseline (mean) | 11 | -29 | 8 | -43
Difference from sulfonylurea alone (adjusted mean) | -- | -42* | -- | -53*
% of patients with ≥30 mg/dL decrease from baseline | 17% | 49% | 15% | 61%
HbAlc (%)
Baseline (mean) | 9.4 | 9.5 | 9.3 | 9.6
Change from baseline (mean) | 0.2 | -1.0 | 0.0 | -1.6
Difference from sulfonylurea alone (adjusted mean) | -- | -1.1* | -- | -1.4*
% of patients with ≥0.7% decrease from baseline | 21% | 60% | 23% | 75%
Once Daily Dosing (3 Studies) | Sulfonylurea | AVANDIA 4 mg once daily + sulfonylurea | Sulfonylurea | AVANDIA 8 mg once daily + sulfonylurea
 | N = 172 | N = 172 | N = 173 | N = 176
FPG (mg/dL)
Baseline (mean) | 198 | 206 | 188 | 192
Change from baseline (mean) | 17 | -25 | 17 | -43
Difference from sulfonylurea alone (adjusted mean) | -- | -47* | -- | -66*
% of patients with ≥30 mg/dL decrease from baseline | 17% | 48% | 19% | 55%
HbAlc (%)
Baseline (mean) | 8.6 | 8.8 | 8.9 | 8.9
Change from baseline (mean) | 0.4 | -0.5 | 0.1 | -1.2
Difference from sulfonylurea alone (adjusted mean) | -- | -0.9* | -- | -1.4*
% of patients with ≥0.7% decrease from baseline | 11% | 36% | 20% | 68%

* p less than 0.0001 compared to sulfonylurea alone.

One of the 24- to 26-week studies included patients who were inadequately controlled on maximal doses of glyburide and switched to 4 mg of AVANDIA daily as monotherapy; in this group, loss of glycemic control was demonstrated, as evidenced by increases in FPG and HbA1c.

In a 2-year double-blind study, elderly patients (aged 59 to 89 years) on half-maximal sulfonylurea (glipizide 10 mg twice daily) were randomized to the addition of AVANDIA (n = 115, 4 mg once daily to 8 mg as needed) or to continued up-titration of glipizide (n = 110), to a maximum of 20 mg twice daily. Mean baseline FPG and HbA1c were 157 mg/dL and 7.72%, respectively, for the AVANDIA plus glipizide arm and 159 mg/dL and 7.65%, respectively, for the glipizide up-titration arm. Loss of glycemic control (FPG ≥180 mg/dL) occurred in a significantly lower proportion of patients (2%) on AVANDIA plus glipizide compared to patients in the glipizide up-titration arm (28.7%). About 78% of the patients on combination therapy completed the 2 years of therapy while only 51% completed on glipizide monotherapy. The effect of combination therapy on FPG and HbA1c was durable over the 2-year study period, with patients achieving a mean of 132 mg/dL for FPG and a mean of 6.98% for HbA1c compared to no change on the glipizide arm.

14.3 Combination With Sulfonylurea Plus Metformin

In two 24- to 26-week, double-blind, placebo-controlled, studies designed to assess the efficacy and safety of AVANDIA in combination with sulfonylurea plus metformin, AVANDIA 4 mg or 8 mg daily, was administered in divided doses twice daily, to patients inadequately controlled on submaximal (10 mg) and maximal (20 mg) doses of glyburide and maximal dose of metformin (2 g/day). A statistically significant improvement in FPG and HbA1c was observed in patients treated with the combinations of sulfonylurea plus metformin and 4 mg of AVANDIA and 8 mg of AVANDIA versus patients continued on sulfonylurea plus metformin, as shown in Table 12.

Table 12. Glycemic Parameters in a 26-Week Combination Study of AVANDIA Plus Sulfonylurea and Metformin
 | Sulfonylurea + metformin | AVANDIA 2 mg twice daily + sulfonylurea + metformin | AVANDIA 4 mg twice daily + sulfonylurea + metformin
 | N = 273 | N =276 | N = 277
FPG (mg/dL)
Baseline (mean) | 189 | 190 | 192
Change from baseline (mean) | 14 | -19 | -40
Difference from sulfonylurea plus metformin (adjusted mean) | -- | -30* | -52*
% of patients with ≥30 mg/dL decrease from baseline | 16% | 46% | 62%
HbAlc (%)
Baseline (mean) | 8.7 | 8.6 | 8.7
Change from baseline (mean) | 0.2 | -0.4 | -0.9
Difference from sulfonylurea plus metformin adjusted mean) | -- | -0.6* | -1.1*
% of patients with ≥0.7% decrease from baseline | 16% | 39% | 63%

* p less than 0.0001 compared to placebo.

15 REFERENCES

1. Food and Drug Administration Briefing Document. Joint meeting of the Endocrinologic and Metabolic Drugs and Drug Safety and Risk Management Advisory Committees. July 30, 2007.
2. DREAM Trial Investigators. Effect of rosiglitazone on the frequency of diabetes in patients with impaired glucose tolerance or impaired fasting glucose: a randomised controlled trial. Lancet 2006;368:1096-1105.
3. Home PD, Pocock SJ, Beck-Nielsen H, et al. Rosiglitazone evaluated for cardiovascular outcomes – an interim analysis. NEJM 2007;357:1-11.
4. Park JY, Kim KA, Kang MH, et al. Effect of rifampin on the pharmacokinetics of rosiglitazone in healthy subjects. Clin Pharmacol Ther 2004;75:157-162.

16 HOW SUPPLIED/STORAGE AND HANDLING

Each pentagonal film-coated TILTAB tablet contains rosiglitazone as the maleate as follows: 2 mg–pink, debossed with SB on one side and 2 on the other; 4 mg–orange, debossed with SB on one side and 4 on the other; 8 mg–red-brown, debossed with SB on one side and 8 on the other.

2 mg bottles of 30: NDC 54868-5249-0
2 mg bottles of 60: NDC 54868-5249-1

4 mg bottles of 30: NDC 54868-4198-0
4 mg bottles of 60: NDC 54868-4198-1

8 mg bottles of 30: NDC 54868-4221-0

Store at 25°C (77°F); excursions 15° to 30°C (59° to 86°F). Dispense in a tight, light-resistant container.

17 PATIENT COUNSELING INFORMATION

17.1 Patient Advice

Patients should be informed of the following:

- AVANDIA is not recommended for patients with symptoms of heart failure.
- Patients with more severe heart failure (NYHA Class 3 or 4) cannot start AVANDIA as the risks exceed any potential benefits in such patients.
- Results of a set of clinical studies suggest that treatment with AVANDIA is associated with an increased risk for myocardial ischemic events, such as angina or myocardial infarction (heart attack), especially in patients taking insulin or nitrates. Because this risk has not been confirmed or excluded in different long-term trials, definitive conclusions regarding this risk await completion of an adequately-designed cardiovascular outcome study.
- AVANDIA is not recommended for patients who are taking nitrates or insulin.
- There are multiple medications available to treat type 2 diabetes. The benefits and risks of each available diabetes medication should be taken into account when choosing a particular diabetes medication for a given patient.
- There have been no clinical studies establishing conclusive evidence of macrovascular risk reduction with AVANDIA or any other oral antidiabetic drug.
- Management of type 2 diabetes should include diet control. Caloric restriction, weight loss, and exercise are essential for the proper treatment of the diabetic patient because they help improve insulin sensitivity. This is important not only in the primary treatment of type 2 diabetes, but in maintaining the efficacy of drug therapy.
- It is important to adhere to dietary instructions and to regularly have blood glucose and glycosylated hemoglobin tested. It can take 2 weeks to see a reduction in blood glucose and 2 to 3 months to see the full effect of AVANDIA.
- Blood will be drawn to check their liver function prior to the start of therapy and periodically thereafter per the clinical judgment of the healthcare professional. Patients with unexplained symptoms of nausea, vomiting, abdominal pain, fatigue, anorexia, or dark urine should immediately report these symptoms to their physician.
- Patients who experience an unusually rapid increase in weight or edema or who develop shortness of breath or other symptoms of heart failure while on AVANDIA should immediately report these symptoms to their physician.
- AVANDIA can be taken with or without meals.
- When using AVANDIA in combination with other hypoglycemic agents, the risk of hypoglycemia, its symptoms and treatment, and conditions that predispose to its development should be explained to patients and their family members.
- Therapy with AVANDIA, like other thiazolidinediones, may result in ovulation in some premenopausal anovulatory women. As a result, these patients may be at an increased risk for pregnancy while taking AVANDIA. Thus, adequate contraception in premenopausal women should be recommended. This possible effect has not been specifically investigated in clinical studies so the frequency of this occurrence is not known.

17.2 FDA-Approved Medication Guide

See separate leaflet.

AVANDIA and TILTAB are registered trademarks of GlaxoSmithKline.

GlaxoSmithKline

Research Triangle Park, NC 27709

©2009, GlaxoSmithKline. All rights reserved.

medication guide

AVANDIA® (ah-VAN-dee-a)

rosiglitazone maleate tablets

Read this Medication Guide carefully before you start taking AVANDIA and each time you get a refill. There may be new information. This information does not take the place of talking with your doctor about your medical condition or your treatment. If you have any questions about AVANDIA, ask your doctor or pharmacist.

What is the most important information I should know about AVANDIA?

AVANDIA is a prescription medicine to treat adults with diabetes. It helps to control high blood sugar. (See “What is AVANDIA?”). It is important that you take AVANDIA exactly how it is prescribed by your doctor to best treat your diabetes.

AVANDIA may cause serious side effects, including:

New or worse heart failure

- AVANDIA can cause your body to keep extra fluid (fluid retention), which leads to swelling (edema) and weight gain. Extra body fluid can make some heart problems worse or lead to heart failure. Heart failure means your heart does not pump blood well enough.
- If you have severe heart failure, you cannot start AVANDIA.
- If you have heart failure with symptoms (such as shortness of breath or swelling), even if these symptoms are not severe, AVANDIA may not be right for you.

Call your doctor right away if you have any of the following:

- swelling or fluid retention, especially in the ankles or legs
- shortness of breath or trouble breathing, especially when you lie down
- an unusually fast increase in weight
- unusual tiredness

Other heart problems

AVANDIA may raise the risk of heart problems related to reduced blood flow to the heart. These include possible increases in the risk of heart-related chest pain (angina) or "heart attack" (myocardial infarction). This risk seemed to be higher in people who took AVANDIA with insulin or with nitrate medicines. Most people who take insulin or nitrate medicines should not also take AVANDIA.

- If you have chest pain or a feeling of chest pressure, get medical help right away, no matter what diabetes medicines you are taking.
- People with diabetes have a greater risk for heart problems. It is important to work with your doctor to manage other conditions, such as high blood pressure or high cholesterol.

AVANDIA can have other serious side effects. Be sure to read the section below “What are possible side effects of AVANDIA?”.

What is AVANDIA?

AVANDIA is a prescription medicine used with diet and exercise to treat adults with type 2 (“adult-onset” or “non-insulin dependent”) diabetes mellitus (“high blood sugar”). AVANDIA helps to control high blood sugar. AVANDIA may be used alone or with other diabetes medicines. AVANDIA can help your body respond better to insulin made in your body. AVANDIA does not cause your body to make more insulin.

- For AVANDIA to work best, it is very important to exercise, lose extra weight, and follow the diet recommended by your doctor.
- AVANDIA has not been studied enough in children under 18 years of age to know if it is safe or effective in children.
- AVANDIA is not for people with type 1 diabetes mellitus or to treat a condition called diabetic ketoacidosis.

Who should not take AVANDIA?

Many people with heart failure should not start taking AVANDIA. See “What should I tell my doctor before taking AVANDIA?”.

What should I tell my doctor before taking AVANDIA?

Before starting AVANDIA, ask your doctor about what the choices are for diabetes medicines, and what the expected benefits and possible risks are for you in particular.

Before taking AVANDIA, tell your doctor about all your medical conditions, including if you:

- have heart problems or heart failure.
- have type 1 (“juvenile”) diabetes or had diabetic ketoacidosis. These conditions should be treated with insulin.
- have a type of diabetic eye disease called macular edema (swelling of the back of the eye).
- have liver problems. Your doctor should do blood tests to check your liver before you start taking AVANDIA and during treatment as needed.
- had liver problems while taking REZULIN® (troglitazone), another medicine for diabetes.
- are pregnant or plan to become pregnant. AVANDIA should not be used during pregnancy. It is not known if AVANDIA can harm your unborn baby. You and your doctor should talk about the best way to control your diabetes during pregnancy. If you are a premenopausal woman (before the “change of life”) who does not have regular monthly periods, AVANDIA may increase your chances of becoming pregnant. Talk to your doctor about birth control choices while taking AVANDIA. Tell your doctor right away if you become pregnant while taking AVANDIA.
- are breast-feeding or planning to breast-feed. It is not known if AVANDIA passes into breast milk. You should not use AVANDIA while breast-feeding.

Tell your doctor about all the medicines you take including prescription and non-prescription medicines, vitamins or herbal supplements. AVANDIA and certain other medicines can affect each other and may lead to serious side effects including high or low blood sugar, or heart problems. Especially tell your doctor if you take:

- insulin.
- nitrate medicines such as nitroglycerin or isosorbide to treat a type of chest pain called angina.
- any medicines for high blood pressure, high cholesterol or heart failure, or for prevention of heart disease or stroke.

Know the medicines you take. Keep a list of your medicines and show it to your doctor and pharmacist before you start a new medicine. They will tell you if it is alright to take AVANDIA with other medicines.

How should I take AVANDIA?

- Take AVANDIA exactly as prescribed. Your doctor will tell you how many tablets to take and how often. The usual daily starting dose is 4 mg a day taken one time each day or 2 mg taken two times each day. Your doctor may need to adjust your dose until your blood sugar is better controlled.
- AVANDIA may be prescribed alone or with other diabetes medicines. This will depend on how well your blood sugar is controlled.
- Take AVANDIA with or without food.
- It can take 2 weeks for AVANDIA to start lowering blood sugar. It may take 2 to 3 months to see the full effect on your blood sugar level.
- If you miss a dose of AVANDIA, take it as soon as you remember, unless it is time to take your next dose. Take your next dose at the usual time. Do not take double doses to make up for a missed dose.
- If you take too much AVANDIA, call your doctor or poison control center right away.
- Test your blood sugar regularly as your doctor tells you.
- Diet and exercise can help your body use its blood sugar better. It is important to stay on your recommended diet, lose extra weight, and get regular exercise while taking AVANDIA.
- Your doctor should do blood tests to check your liver before you start AVANDIA and during treatment as needed. Your doctor should also do regular blood sugar tests (for example, “A1C”) to monitor your response to AVANDIA.

What are possible side effects of AVANDIA?

AVANDIA may cause serious side effects including:

- New or worse heart failure. See “What is the most important information I should know about AVANDIA?”.
- Other heart problems. AVANDIA may increase the risk of heart problems related to reduced blood flow to the heart. These include possible increases in the risk of heart-related chest pain (angina) or "heart attack" (myocardial infarction). See “What is the most important information I should know about AVANDIA?”.
- Swelling (edema). AVANDIA can cause swelling due to fluid retention. See “What is the most important information I should know about AVANDIA?”.
- Weight gain. AVANDIA can cause weight gain that may be due to fluid retention or extra body fat. Weight gain can be a serious problem for people with certain conditions including heart problems. See “What is the most important information I should know about AVANDIA?”.
- Liver problems. It is important for your liver to be working normally when you take AVANDIA. Your doctor should do blood tests to check your liver before you start taking AVANDIA and during treatment as needed. Call your doctor right away if you have unexplained symptoms such as:
  - nausea or vomiting
  - stomach pain
  - unusual or unexplained tiredness
  - loss of appetite
  - dark urine
  - yellowing of your skin or the whites of your eyes.
- Macular edema (a diabetic eye disease with swelling in the back of the eye). Tell your doctor right away if you have any changes in your vision. Your doctor should check your eyes regularly. Very rarely, some people have experienced vision changes due to swelling in the back of the eye while taking AVANDIA.
- Fractures (broken bones), usually in the hand, upper arm or foot, in females. Talk to your doctor for advice on how to keep your bones healthy.
- Low red blood cell count (anemia).
- Low blood sugar (hypoglycemia). Lightheadedness, dizziness, shakiness or hunger may mean that your blood sugar is too low. This can happen if you skip meals, if you use another medicine that lowers blood sugar, or if you have certain medical problems. Call your doctor if low blood sugar levels are a problem for you.
- Ovulation (release of egg from an ovary in a woman) leading to pregnancy. Ovulation may happen in premenopausal women who do not have regular monthly periods. This can increase the chance of pregnancy. See “What should I tell my doctor before taking AVANDIA?”.

The most common side effects of AVANDIA reported in clinical trials included cold-like symptoms and headache.

Call your doctor for medical advice about side effects. You may report side effects to FDA at 1-800-FDA-1088.

How should I store AVANDIA?

- Store AVANDIA at room temperature, 59° to 86°F (15° to 30°C). Keep AVANDIA in the container it comes in.
- Safely, throw away AVANDIA that is out of date or no longer needed.
- Keep AVANDIA and all medicines out of the reach of children.

General information about AVANDIA

Medicines are sometimes prescribed for purposes other than those listed in a Medication Guide. Do not use AVANDIA for a condition for which it was not prescribed. Do not give AVANDIA to other people, even if they have the same symptoms you have. It may harm them.

This Medication Guide summarizes important information about AVANDIA. If you would like more information, talk with your doctor. You can ask your doctor or pharmacist for information about AVANDIA that is written for healthcare professionals. You can also find out more about AVANDIA by calling 1-888-825-5249 or visiting the website www.avandia.com.

What are the ingredients in AVANDIA?

Active Ingredient: Rosiglitazone maleate.

Inactive Ingredients: Hypromellose 2910, lactose monohydrate, magnesium stearate, microcrystalline cellulose, polyethylene glycol 3000, sodium starch glycolate, titanium dioxide, triacetin, and 1 or more of the following: Synthetic red and yellow iron oxides and talc.

Always check to make sure that the medicine you are taking is the correct one. AVANDIA tablets are triangles with rounded corners and look like this:

2 mg strength tablets – pink with “SB” on one side and “2” on the other.

4 mg strength tablets – orange with “SB” on one side and “4” on the other.

8 mg strength tablets – red-brown with “SB” on one side and “8” on the other.

AVANDIA is a registered trademark of GlaxoSmithKline.

REZULIN is a registered trademark of Parke-Davis Pharmaceuticals Ltd.

This Medication Guide has been approved by the U.S. Food and Drug Administration.

GlaxoSmithKline

Research Triangle Park, NC 27709

©2008, GlaxoSmithKline. All rights reserved.

October 2008

AVD:4MG

PRINCIPAL DISPLAY PANEL

AVANDIA®

ROSIGLITAZONE MALEATE TABLETS

2 mg

AVANDIA®

ROSIGLITAZONE MALEATE TABLETS

4 mg

AVANDIA®

ROSIGLITAZONE MALEATE TABLETS

8 mg